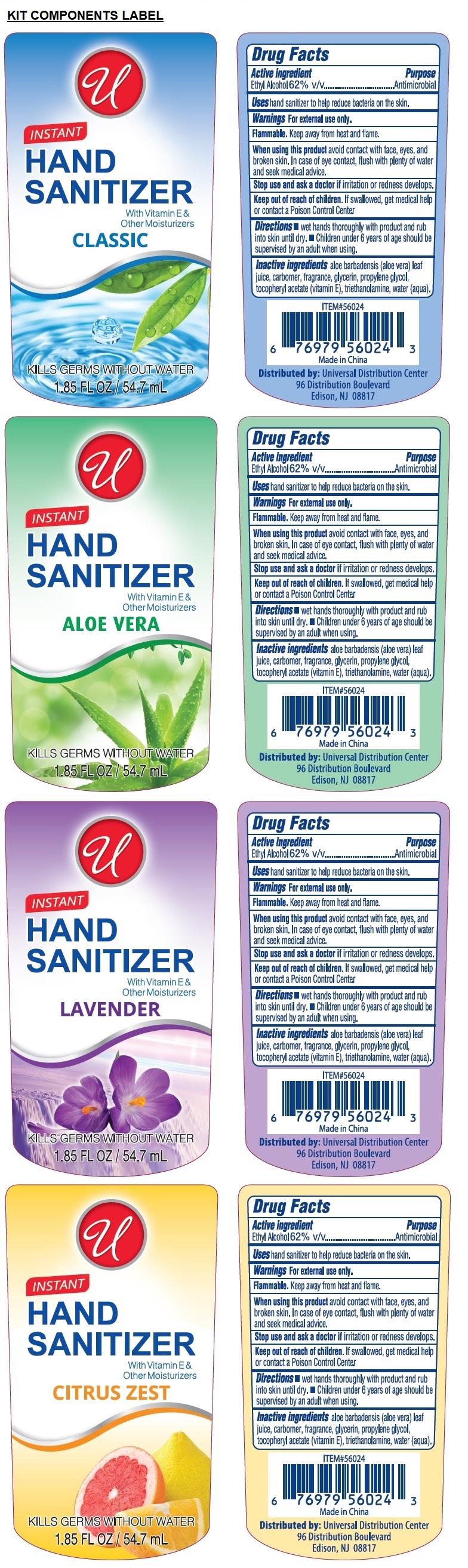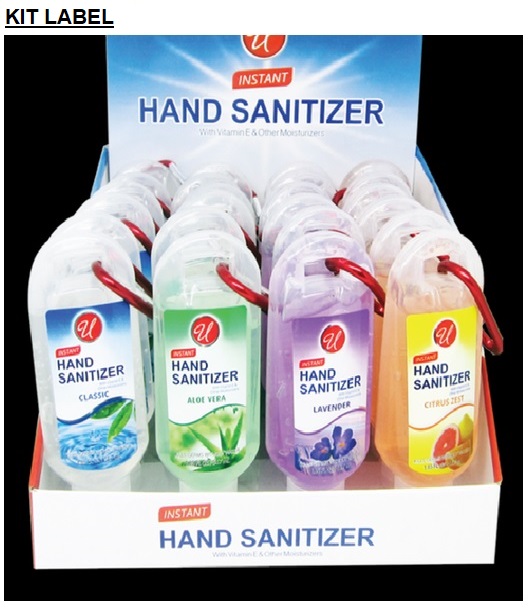 DRUG LABEL: W/CLIP PDQ HAND SANITIZER
NDC: 52000-127 | Form: KIT | Route: TOPICAL
Manufacturer: Universal Distribution Center LLC
Category: otc | Type: HUMAN OTC DRUG LABEL
Date: 20211203

ACTIVE INGREDIENTS: ALCOHOL 0.62 mL/1 mL; ALCOHOL 0.62 mL/1 mL; ALCOHOL 0.62 mL/1 mL; ALCOHOL 0.62 mL/1 mL
INACTIVE INGREDIENTS: ALOE VERA LEAF; CARBOMER HOMOPOLYMER, UNSPECIFIED TYPE; GLYCERIN; PROPYLENE GLYCOL; .ALPHA.-TOCOPHEROL ACETATE; TROLAMINE; WATER; ALOE VERA LEAF; CARBOMER HOMOPOLYMER, UNSPECIFIED TYPE; GLYCERIN; PROPYLENE GLYCOL; .ALPHA.-TOCOPHEROL ACETATE; TROLAMINE; WATER; ALOE VERA LEAF; CARBOMER HOMOPOLYMER, UNSPECIFIED TYPE; GLYCERIN; PROPYLENE GLYCOL; .ALPHA.-TOCOPHEROL ACETATE; TROLAMINE; WATER; ALOE VERA LEAF; CARBOMER HOMOPOLYMER, UNSPECIFIED TYPE; GLYCERIN; PROPYLENE GLYCOL; .ALPHA.-TOCOPHEROL ACETATE; TROLAMINE; WATER

W/CLIP PDQ HAND SANITIZER

Active ingredient

Ethyl Alcohol 62% V/V

Purpose

Antimicrobial

Uses

hand sanitizer to help reduce bacteria on the skin.

Warnings

For external use only.

Flammable. Keep away from heat and flame.

When using this product avoid contact with face, eyes, and broken skin. In case of eye contact, flush with plenty of water and seek medical advice.

Stop use and ask a doctor if irritation or redness develops.

Keep out of reach of children. If swallowed, get medical help or contact a Poison Control Center

Directions

• wet hands thoroughly with product and rub into skin until dry. • Children under 6 years of age should be supervised by an adult when using.

Inactive ingredients

aloe barbadensis (aloe vera) leaf juice, carbomer, fragrance, glycerin, propylene glycol, tocopheryl acetate (vitamin E), triethanolamine, water (aqua).

INSTANT HAND SANITIZER

with Vitamin E & Other Moisturizers

CLASSIC

ALOE VERA

LAVENDER

CITRUS ZEST

KILLS GERMS WITHOUT WATER

Made in China

Distributed by: Universal Distribution Center
96 Distribution Boulevard
Edison, NJ 08817